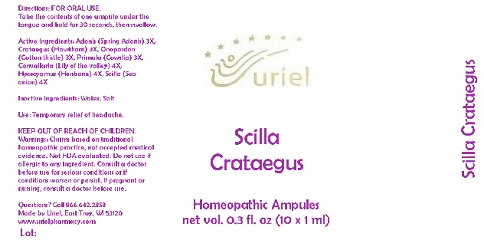 DRUG LABEL: Scilla Crataegus
NDC: 48951-8166 | Form: LIQUID
Manufacturer: Uriel Pharmacy Inc.
Category: homeopathic | Type: HUMAN OTC DRUG LABEL
Date: 20180524

ACTIVE INGREDIENTS: ADONIS VERNALIS FLOWERING TOP 3 [hp_X]/1 mL; HAWTHORN LEAF WITH FLOWER 3 [hp_X]/1 mL; ONOPORDUM ACANTHIUM FLOWER 3 [hp_X]/1 mL; PRIMULA VERIS FLOWER 3 [hp_X]/1 mL; CONVALLARIA MAJALIS 4 [hp_X]/1 mL; HYOSCYAMUS NIGER LEAF 4 [hp_X]/1 mL; DRIMIA MARITIMA BULB 4 [hp_X]/1 mL
INACTIVE INGREDIENTS: WATER; SODIUM CHLORIDE

Scilla Crataegus

INDICATIONS AND USAGE

Directions: FOR ORAL USE.

DOSAGE AND ADMINISTRATION

Take the contents of one ampule under the tongue and hold for 30 seconds, then swallow.

ACTIVE INGREDIENT

Active Ingredients: Adonis ex herba 3X, Crataegus e fol. et fruct. 3X, Onopordon e flor. 3X, Primula e flor. 3X, Convallaria e pl. tota 4X, Hyoscyamus ex herba 4X, Scilla e bulbo 4X

Inactive Ingredients: Water, Salt

PURPOSE

Use: Temporary relief of headache.

KEEP OUT OF REACH OF CHILDREN.

WARNINGS

Warnings: Claims based on traditional homeopathic practice, not accepted medical evidence. Not FDA evaluated. Do not use if allergic to any ingredient. Consult a doctor before use for serious conditions or if conditions worsen or persist. If pregnant or nursing, consult a doctor before use.

QUESTIONS

Questions? Call 866.642.2858 Made by Uriel, East Troy, WI 53120 www.urielpharmacy.com